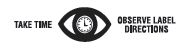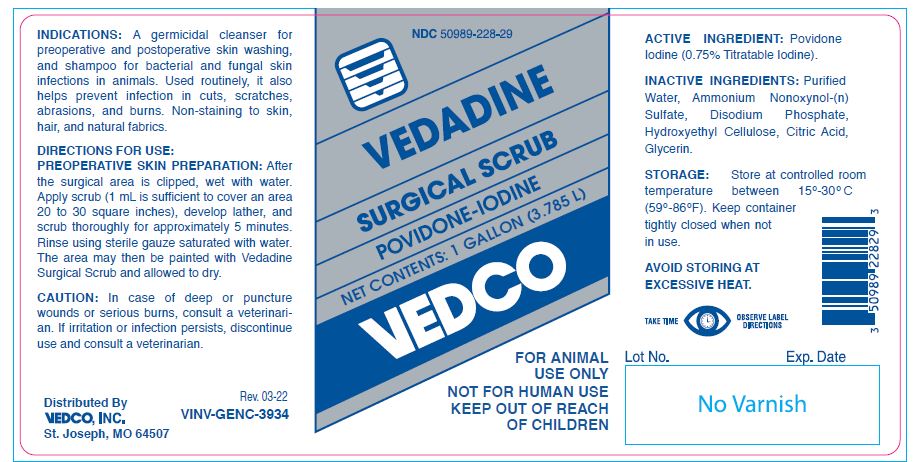 DRUG LABEL: VEDADINE
NDC: 50989-228 | Form: SOLUTION
Manufacturer: Vedco, Inc.
Category: animal | Type: OTC ANIMAL DRUG LABEL
Date: 20250505

ACTIVE INGREDIENTS: POVIDONE-IODINE 5.1 g/1 L

VEDADINE
SURGICAL SCRUB
POVIDONE-IODINE

KEEP OUT OF REACH OF CHILDREN

FOR ANIMAL USE ONLY
NOT FOR HUMAN USE
KEEP OUT OF REACH OF CHILDREN

INDICATIONS:

A germicidal cleanser for preoperative and postoperative skin washing, and shampoo for bacterial and fungal skin infections in animals. Used routinely, it also helps prevent infection in cuts, scratches, abrasions, and burns. Non-staining to skin, hair, and natural fabrics.

DIRECTIONS FOR USE:

PREOPERATIVE SKIN PREPARATION: After the surgical area is clipped, wet with water. Apply scrub (1 mL is sufficient to cover an area 20 to 30 square inches), develop lather, and scrub thoroughly for approximately 5 minutes. Rinse using sterile gauze saturated with water. The area may then be painted with Vedadine Surgical Scrub and allowed to dry.

CAUTION:

In case of deep or puncture wounds or serious burns, consult a veterinarian. If irritation or infection persists, discontinue use and consult a veterinarian.

ACTIVE INGREDIENT:

Povidone Iodine (0.75% Titratable Iodine).

INACTIVE INGREDIENTS:

Purified Water, Ammonium Nonoxynol-(n) Sulfate, Disodium Phosphate, Hydroxyethyl Cellulose, Citric Acid, Glycerin.

STORAGE:

Store at controlled room temperature between 15º-30ºC (59º-86ºF). Keep container tightly closed when not in use.

AVOID STORING AT EXCESSIVE HEAT.

NET CONTENTS:

1 GALLON (3.785 L) VINV-GENC-3934

INFORMATION FOR OWNERS/CAREGIVERS

Distributed By
VEDCO, INC.
St. Joseph, MO 64507